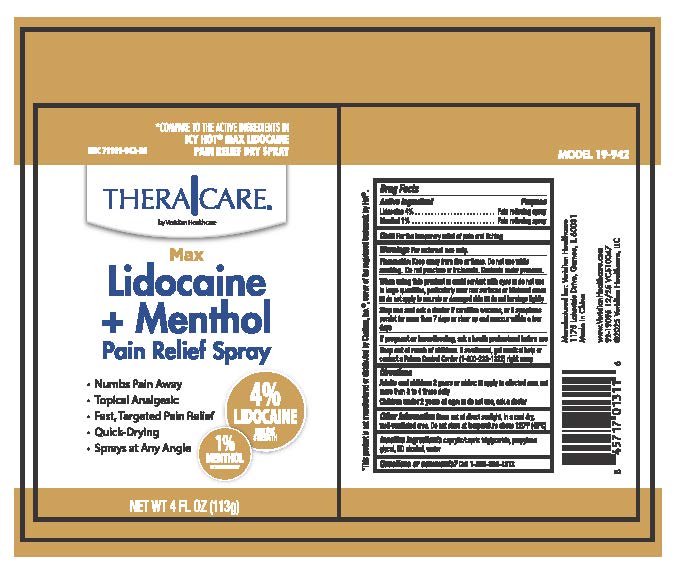 DRUG LABEL: TheraCare Lidocaine plus Menthol
NDC: 71101-942 | Form: SPRAY
Manufacturer: Veridian Healthcare
Category: otc | Type: HUMAN OTC DRUG LABEL
Date: 20260105

ACTIVE INGREDIENTS: LIDOCAINE 4 g/1 mL; MENTHOL 1 g/1 mL
INACTIVE INGREDIENTS: ALCOHOL 95%; WATER; PROPYLENE GLYCOL; CAPRYLIC/CAPRIC TRIGLYCERIDE

TheraCare Lidocaine + Menthol Pain Relief Spray

Drug Facts

Lidocaine Menthol

Purpose

Pain relieving spray

Uses

for temporary relief of pain and itching

Warnings

For external use only

Flammable Do not use while smoking or near heat of flame. Do not use while smoking. Do not punture or incinerate. Contents under pressure

Stop use and ask a doctor

- if condition worsens or if symptoms persist for more than 7 days or clear up and reoccur withing a few days

When using this product

- avoid contact with eyes
- do not use in large quantities, particulary over raw surfaces or blistered areas
- do not apply to wounds or damage skin
- do not bandage tightly

Stop use and ask a doctor if

- condition worsens
- symptoms persist for more than 7 days symptoms or clear up and reoccur within a few days

Keep out of reach of children.

If swallowed, get medical help or contact a Poison Control Center (1-800-222-1222) right away.

Directions

- adults and children 2 years and older:apply to affected area not more than 3 to 4 times daily.
- children under 2 years of age:do not use, ask a doctor

Other information

- Store out of direct sunlight, in a cool dry well-ventilated area
- Do not store at temperature above 120F (49C)

Inactive ingredients

caprylic/capric triglyceride, propylene glycol, SD alcohol, water